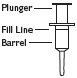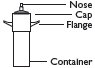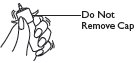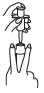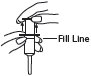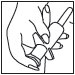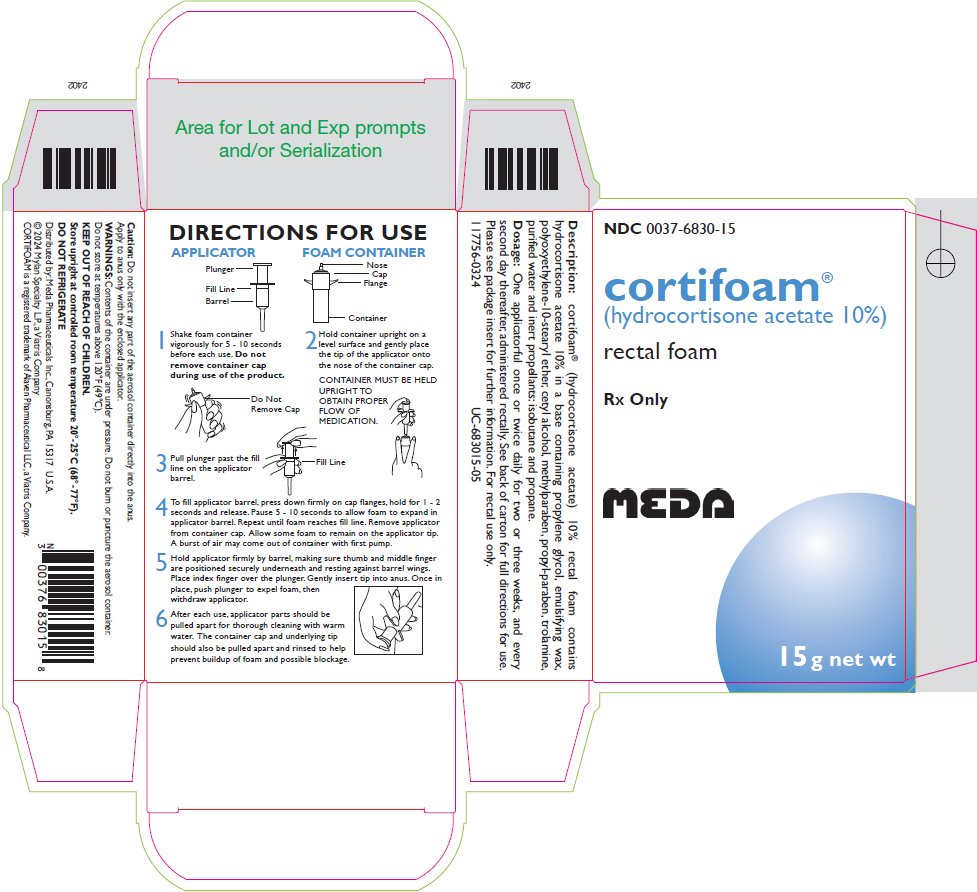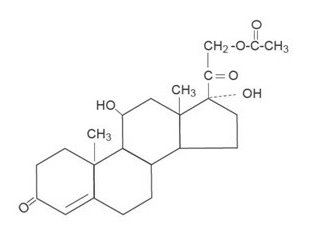 DRUG LABEL: Cortifoam
NDC: 0037-6830 | Form: AEROSOL, FOAM
Manufacturer: Viatris Specialty LLC
Category: prescription | Type: HUMAN PRESCRIPTION DRUG LABEL
Date: 20240515

ACTIVE INGREDIENTS: HYDROCORTISONE ACETATE 1500 mg/15 g
INACTIVE INGREDIENTS: PROPYLENE GLYCOL; ETHYLENE DISTEARAMIDE; STEARETH-10; CETYL ALCOHOL; METHYLPARABEN; PROPYLPARABEN; TROLAMINE; WATER; ISOBUTANE; PROPANE

DESCRIPTION

Cortifoam® (hydrocortisone acetate rectal aerosol) 10% Rectal Foam contains hydrocortisone acetate 10% in a base containing propylene glycol, emulsifying wax, polyoxyethylene-10-stearyl ether, cetyl alcohol, methylparaben, propylparaben, trolamine, purified water and inert propellants: isobutane and propane.

Each application delivers approximately 900 mg of foam containing 80 mg of hydrocortisone (90 mg of hydrocortisone acetate).

The molecular weight of hydrocortisone acetate is 404.50. It is designated chemically as pregn-4-ene-3,20-dione,21-(acetyloxy)-11,17-dihydroxy-,(11β)-. The empirical formula is C23H32O6 and the structural formula is:

Hydrocortisone acetate, a synthetic adrenocortical steroid, is a white to practically white, odorless, crystalline powder. It is insoluble in water (1 mg/100 mL) and slightly soluble in alcohol and chloroform.

CLINICAL PHARMACOLOGY

Cortifoam® provides effective topical administration of an anti-inflammatory corticosteroid as adjunctive therapy of ulcerative proctitis. Direct observations of methylene blue-containing foam have shown staining about 10 centimeters into the rectum.

INDICATIONS AND USAGE

Cortifoam® is indicated as adjunctive therapy in the topical treatment of ulcerative proctitis of the distal portion of the rectum in patients who cannot retain hydrocortisone or other corticosteroid enemas.

CONTRAINDICATIONS

Cortifoam® is contraindicated in patients who are hypersensitive to any components of this product.

Local contraindications to the use of intrarectal steroids include obstruction, abscess, perforation, peritonitis, fresh intestinal anastomoses, extensive fistulas and sinus tracts.

WARNINGS

General

Do not insert any part of the aerosol container directly into the anus. Contents of the container are under pressure. Do not burn or puncture the aerosol container. Do not store at temperatures above 120°F. Because Cortifoam® is not expelled, systemic hydrocortisone absorption may be greater from Cortifoam® than from corticosteroid enema formulations. If there is not evidence of clinical or proctologic improvement within two or three weeks after starting Cortifoam® therapy, or if the patient's condition worsens, discontinue the drug.

Rare instances of anaphylactoid reactions have occurred in patients receiving corticosteroid therapy (see ADVERSE REACTIONS).

Cardio-renal

Corticosteroids can cause elevation of blood pressure, salt and water retention, and increased excretion of potassium. These effects are less likely to occur with the synthetic derivatives except when used in large doses. Dietary salt restriction and potassium supplementation may be necessary. All corticosteroids increase calcium excretion.

Literature reports suggest an apparent association between use of corticosteroids and left ventricular free wall rupture after a recent myocardial infarction; therefore, therapy with corticosteroids should be used with great caution in these patients.

Endocrine

Corticosteroids can produce reversible hypothalamicpituitary adrenal (HPA) axis suppression with the potential for glucocorticosteroid insufficiency after withdrawal of treatment.

Metabolic clearance of corticosteroids is decreased in hypothyroid patients and increased in hyperthyroid patients. Changes in thyroid status of the patient may necessitate adjustment in dosage.

Infections

General

Patients who are on corticosteroids are more susceptible to infections than are healthy individuals. There may be decreased resistance and inability to localize infection when corticosteroids are used. Infection with any pathogen (viral, bacterial, fungal, protozoan or helminthic) in any location of the body may be associated with the use of corticosteroids alone or in combination with other immunosuppressive agents. These infections may be mild to severe. With increasing doses of corticosteroids, the rate of occurrence of infectious complications increases. Corticosteroids may also mask some signs of current infection.

Fungal infections

Corticosteroids may exacerbate systemic fungal infections and therefore should not be used in the presence of such infections unless they are needed to control drug reactions. There have been cases reported in which concomitant use of amphotericin B and hydrocortisone was followed by cardiac enlargement and congestive heart failure (see PRECAUTIONS, Drug Interactions, Amphotericin B injection and potassium-depleting agents).

Special pathogens

Latent disease may be activated or there may be an exacerbation of intercurrent infections due to pathogens, including those caused by Amoeba, Candida, Cryptococcus, Mycobacterium, Nocardia, Pneumocystis, and Toxoplasma.

It is recommended that latent amebiasis or active amebiasis be ruled out before initiating corticosteroid therapy in any patient who has spent time in the tropics or in any patient with unexplained diarrhea.

Similarly, corticosteroids should be used with great care in patients with known or suspected Strongyloides (thread worm) infestation. In such patients, corticosteroid-induced immunosuppression may lead to Strongyloides hyperinfection and dissemination with widespread larval migration, often accompanied by severe enterocolitis and potentially fatal gram-negative septicemia.

Corticosteroids should not be used in cerebral malaria.

Tuberculosis

If corticosteroids are indicated in patients with latent tuberculosis or tuberculin reactivity, close observation is necessary as reactivation of the disease may occur. During prolonged corticosteroid therapy, these patients should receive chemoprophylaxis.

Vaccination

Administration of live or live, attenuated vaccines is contraindicated in patients receiving immunosuppressive doses of corticosteroids. Killed or inactivated vaccines may be administered. However, the response to such vaccines cannot be predicted. Immunization procedures may be undertaken in patients who are receiving corticosteroids as replacement therapy, e.g., for Addison's disease.

Viral infections

Chickenpox and measles can have a more serious or even fatal course in pediatric and adult patients on corticosteroids. In pediatric and adult patients who have not had these diseases, particular care should be taken to avoid exposure. The contribution of the underlying disease and/or prior corticosteroid treatment to the risk is also not known. If exposed to chickenpox, prophylaxis with varicella zoster immune globulin (VZIG) may be indicated. If exposed to measles, prophylaxis with immunoglobulin (IG) may be indicated. (See the respective package inserts for complete VZIG and IG prescribing information.) If chickenpox develops, treatment with antiviral agents should be considered.

Ophthalmic

Use of corticosteroids may produce posterior subcapsular cataracts, glaucoma with possible damage to the optic nerves, and may enhance the establishment of secondary ocular infections due to bacteria, fungi, or viruses. If a patient presents with symptoms such as blurred vision or other visual disturbances, the patient should be considered for referral to an ophthalmologist for evaluation. The use of oral corticosteroids is not recommended in the treatment of optic neuritis and may lead to an increase in the risk of new episodes. Corticosteroids should not be used in active ocular herpes simplex.

PRECAUTIONS

General

The lowest possible dose of corticosteroid should be used to control the condition under treatment. When reduction in dosage is possible, the reduction should be gradual.

Since complications of treatment with glucocorticoids are dependent on the size of the dose and the duration of treatment, a risk/benefit decision must be made in each individual case as to dose and duration of treatment and as to whether daily or intermittent therapy should be used.

Kaposi's sarcoma has been reported to occur in patients receiving corticosteroid therapy, most often for chronic conditions. Discontinuation of corticosteroids may result in clinical improvement.

Cardio-renal

As sodium retention with resultant edema and potassium loss may occur in patients receiving corticosteroids, these agents should be used with caution in patients with congestive heart failure, hypertension, or renal insufficiency.

Endocrine

Drug-induced secondary adrenocortical insufficiency may be minimized by gradual reduction of dosage. This type of relative insufficiency may persist for months after discontinuation of therapy; therefore, in any situation of stress occurring during that period, hormone therapy should be reinstituted. Since mineralocorticoid secretion may be impaired, salt and/or a mineralocorticoid should be administered concurrently.

Gastrointestinal

Steroids should be used with caution in active or latent peptic ulcers, diverticulitis, fresh intestinal anastomoses, and nonspecific ulcerative colitis, since they may increase the risk of a perforation. Where surgery is imminent, it is hazardous to wait more than a few days for a satisfactory response to medical treatment.

Do not employ in immediate or early postoperative period following ileorectostomy.

Signs of peritoneal irritation following gastrointestinal perforation in patients receiving corticosteroids may be minimal or absent.

There is an enhanced effect of corticosteroids in patients with cirrhosis.

Musculoskeletal

Corticosteroids decrease bone formation and increase bone resorption both through their effect on calcium regulation (i.e., decreasing absorption and increasing excretion) and inhibition of osteoblast function. This, together with a decrease in the protein matrix of the bone secondary to an increase in protein catabolism, and reduced sex hormone production, may lead to inhibition of bone growth in pediatric patients and the development of osteoporosis at any age. Special consideration should be given to patients at increased risk of osteoporosis (i.e., postmenopausal women) before initiating corticosteroid therapy.

Neuro-psychiatric

An acute myopathy has been observed with the use of high doses of corticosteroids, most often occurring in patients with disorders of neuromuscular transmission (e.g., myasthenia gravis), or in patients receiving concomitant therapy with neuromuscular blocking drugs (e.g., pancuronium). This acute myopathy is generalized, may involve ocular and respiratory muscles, and may result in quadriparesis. Elevation of creatinine kinase may occur. Clinical improvement or recovery after stopping corticosteroids may require weeks to years.

Psychic derangements may appear when corticosteroids are used, ranging from euphoria, insomnia, mood swings, personality changes, and severe depression to frank psychotic manifestations. Also, existing emotional instability or psychotic tendencies may be aggravated by corticosteroids.

Ophthalmic

Intraocular pressure may become elevated in some individuals. If steroid therapy is continued for more than 6 weeks, intraocular pressure should be monitored.

Information for Patients

Patients should be warned not to discontinue the use of corticosteroids abruptly or without medical supervision, to advise any medical attendants that they are taking corticosteroids and to seek medical advice at once should they develop fever or other signs of infection.

Persons who are on corticosteroids should be warned to avoid exposure to chickenpox or measles. Patients should also be advised that if they are exposed, medical advice should be sought without delay.

Drug Interactions

Aminoglutethimide: Aminoglutethimide may lead to a loss of corticosteroid-induced adrenal suppression.

Amphotericin B injection and potassium-depleting agents: When corticosteroids are administered concomitantly with potassium-depleting agents (i.e., amphotericin B, diuretics), patients should be observed closely for development of hypokalemia. There have been cases reported in which concomitant use of amphotericin B and hydrocortisone was followed by cardiac enlargement and congestive heart failure.

Antibiotics: Macrolide antibiotics have been reported to cause a significant decrease in corticosteroid clearance.

Anticholinesterases: Concomitant use of anticholinesterase agents and corticosteroids may produce severe weakness in patients with myasthenia gravis. If possible, anticholinesterase agents should be withdrawn at least 24 hours before initiating corticosteroid therapy.

Anticoagulants, oral: Coadministration of corticosteroids and warfarin result in inhibition of response to warfarin. Therefore, coagulation indices should be monitored to maintain the desired anticoagulant effect.

Antidiabetics: Because corticosteroids may increase blood glucose concentrations, dosage adjustments of antidiabetic agents may be required.

Antitubercular drugs: Serum concentrations of isoniazid may be decreased.

Cholestyramine: Cholestyramine may increase the clearance of corticosteroids.

Cyclosporine: Increased activity of both cyclosporine and corticosteroids may occur when the two are used concurrently. Convulsions have been reported with this concurrent use.

Digitalis glycosides: Patients on digitalis glycosides may be at increased risk of arrhythmias due to hypokalemia.

Estrogens, including oral contraceptives: Estrogens may decrease the hepatic metabolism of certain corticosteroids, thereby increasing their effect.

Hepatic Enzyme Inducers (e.g., barbiturates, phenytoin, carbamazepine, rifampin): Drugs which induce hepatic microsomal drug metabolizing enzyme activity may enhance the metabolism of corticosteroids and require that the dosage of the corticosteroid be increased.

Ketoconazole: Ketoconazole has been reported to decrease the metabolism of certain corticosteroids by up to 60%, leading to an increased risk of corticosteroids side effects.

Nonsteroidal anti-inflammatory agents (NSAIDS): Concomitant use of aspirin (or other nonsteroidal anti-inflammatory agents) and corticosteroids increases the risk of gastrointestinal side effects. Aspirin should be used cautiously in conjunction with corticosteroids in hypoprothrombinemia. The clearance of salicylates may be increased with concurrent use of corticosteroids.

Skin tests: Corticosteroids may suppress reactions to skin tests.

Vaccines: Patients on prolonged corticosteroid therapy may exhibit a diminished response to toxoids and live or inactivated vaccines due to inhibition of antibody response. Corticosteroids may also potentiate the replication of some organisms contained in live attenuated vaccines. Routine administration of vaccines or toxoids should be deferred until corticosteroid therapy is discontinued if possible (see WARNINGS, Infections, Vaccination).

Carcinogenesis, Mutagenesis, Impairment of Fertility

No adequate studies have been conducted in animals to determine whether corticosteroids have a potential for carcinogenesis or mutagenesis.

Steroids may increase or decrease motility and number of spermatozoa in some patients.

Pregnancy

Teratogenic Effects

Corticosteroids have been shown to be teratogenic in many species when given in doses equivalent to the human dose. Animal studies in which corticosteroids have been given to pregnant mice, rats, and rabbits have yielded an increased incidence of cleft palate in the offspring. There are no adequate and well-controlled studies in pregnant women. Corticosteroids should be used during pregnancy only if the potential benefit justifies the potential risk to the fetus. Infants born to mothers who have received corticosteroids during pregnancy should be carefully observed for signs of hypoadrenalism.

Nursing Mothers

Systemically administered corticosteroids appear in human milk and could suppress growth, interfere with endogenous corticosteroid production, or cause other untoward effects. Caution should be exercised when corticosteroids are administered to a nursing woman.

Pediatric Use

Safety and effectiveness in pediatric patients have not been established.

Geriatric Use

No overall differences in safety or effectiveness were observed between elderly subjects and younger subjects, and other reported clinical experience has not identified differences in responses between the elderly and younger patients, but greater sensitivity of some older individuals cannot be ruled out.

ADVERSE REACTIONS

(listed alphabetically, under each subsection)

To report SUSPECTED ADVERSE REACTIONS, contact Meda Pharmaceuticals Inc. at 1-877-848-6608 or
FDA at 1-800-FDA-1088 or www.fda.gov/medwatch.

Allergic reactions: Anaphylactoid reaction, anaphylaxis, angioedema.

Cardiovascular: Bradycardia, cardiac arrest, cardiac arrhythmias, cardiac enlargement, circulatory collapse, congestive heart failure, fat embolism, hypertension, hypertrophic cardiomyopathy in premature infants, myocardial rupture following recent myocardial infarction (see WARNINGS), pulmonary edema, syncope, tachycardia, thromboembolism, thrombophlebitis, vasculitis.

Dermatologic: Acne, allergic dermatitis, cutaneous and subcutaneous atrophy, dry scaly skin, ecchymoses and petechiae, edema, erythema, hyperpigmentation, hypopigmentation, impaired wound healing, increased sweating, rash, sterile abscess, striae, suppressed reactions to skin tests, thin fragile skin, thinning scalp hair, urticaria.

Endocrine: Decreased carbohydrate and glucose tolerance, development of cushingoid state, glycosuria, hirsutism, hypertrichosis, increased requirements for insulin or oral hypoglycemic agents in diabetes, manifestations of latent diabetes mellitus, menstrual irregularities, secondary adrenocortical and pituitary unresponsiveness (particularly in times of stress, as in trauma, surgery, or illness), suppression of growth in pediatric patients.

Fluid and electrolyte disturbances: Congestive heart failure in susceptible patients, fluid retention, hypokalemic alkalosis, potassium loss, sodium retention.

Where hypokalemia and other symptoms associated with fluid and electrolyte imbalance call for potassium supplementation and salt poor or salt-free diets, these may be instituted and are compatible with diet requirements for ulcerative proctitis.

Gastrointestinal: Abdominal distention, elevation in serum liver enzyme levels (usually reversible upon discontinuation), hepatomegaly, increased appetite, nausea, pancreatitis, peptic ulcer with possible perforation and hemorrhage, perforation of the small and large intestine (particularly in patients with inflammatory bowel disease), ulcerative esophagitis.

Metabolic: Negative nitrogen balance due to protein catabolism.

Musculoskeletal: Aseptic necrosis of femoral and humeral heads, Charcot-like arthropathy, loss of muscle mass, muscle weakness, osteoporosis, pathologic fracture of long bones, steroid myopathy, tendon rupture, vertebral compression fractures.

Neurologic/Psychiatric: Convulsions, depression, emotional instability, euphoria, headache, increased intracranial pressure with papilledema (pseudotumor cerebri) usually following discontinuation of treatment, insomnia, mood swings, neuritis, neuropathy, paresthesia, personality changes, psychic disorders, vertigo.

Ophthalmic: Blurred vision, exophthalmos, glaucoma, increased intraocular pressure, posterior subcapsular cataracts, rare instances of blindness associated with periocular injections.

Other: Abnormal fat deposits, decreased resistance to infection, hiccups, increased or decreased motility and number of spermatozoa, malaise, moon face, weight gain.

OVERDOSAGE

Treatment of acute overdosage is by supportive and symptomatic therapy. For chronic overdosage in the face of severe disease requiring continuous steroid therapy, the dosage of the corticosteroid may be reduced only temporarily, or alternate day treatment may be introduced.

DOSAGE AND ADMINISTRATION

The usual dose is one applicatorful once or twice daily for two or three weeks, and every second day thereafter, administered rectally. Directions for use, below and on the carton, describe how to use the aerosol container and applicator. Satisfactory response usually occurs within five to seven days marked by a decrease in symptoms. Symptomatic improvement in ulcerative proctitis should not be used as the sole criterion for evaluating efficacy. Sigmoidoscopy is also recommended to judge dosage adjustment, duration of therapy, and rate of improvement.

It Should Be Emphasized that Dosage Requirements are Variable and Must Be Individualized on the Basis of the Disease Under Treatment and the Response of the Patient. After a favorable response is noted, the proper maintenance dosage should be determined by decreasing the initial drug dosage in small decrements at appropriate time intervals until the lowest dosage which will maintain an adequate clinical response is reached. Situations which may make dosage adjustments necessary are changes in clinical status secondary to remissions or exacerbations in the disease process, the patient's individual drug responsiveness, and the effect of patient exposure to stressful situations not directly related to the disease entity under treatment. In this latter situation it may be necessary to increase the dosage of the corticosteroid for a period of time consistent with the patient's condition. If after long-term therapy the drug is to be stopped, it is recommended that it be withdrawn gradually rather than abruptly.

Directions For Use

(1) Shake foam container vigorously for 5-10 seconds before each use. Do not remove container cap during use of the product.

(2) Hold container upright on a level surface and gently place the tip of the applicator onto the nose of the container cap. CONTAINER MUST BE HELD UPRIGHT TO OBTAIN PROPER FLOW OF MEDICATION.

(3) Pull plunger past the fill line on the applicator barrel.

(4) To fill applicator barrel, press down firmly on cap flanges, hold for 1 – 2 seconds and release. Pause 5 – 10 seconds to allow foam to expand in applicator barrel. Repeat until foam reaches fill line. Remove applicator from container cap. Allow some foam to remain on the applicator tip. A burst of air may come out of container with first pump.

(5) Hold applicator firmly by barrel, making sure thumb and middle finger are positioned securely underneath and resting against barrel wings. Place index finger over the plunger. Gently insert tip into anus. Once in place, push plunger to expel foam, then withdraw applicator.

CAUTION: Do not insert any part of the aerosol container directly into the anus. Apply to anus only with enclosed applicator.

(6) After each use, applicator parts should be pulled apart for thorough cleaning with warm water. The container cap and underlying tip should also be pulled apart and rinsed to help prevent build-up of foam and possible blockage.

HOW SUPPLIED

Cortifoam® is supplied in an aerosol container with a special rectal applicator. Each applicator delivers approximately 900 mg of foam containing approximately 80 mg of hydrocortisone as 90 mg of hydrocortisone acetate. When used correctly, the aerosol container will deliver a minimum of 14 applications.

NDC 0037-6830-15 15 g

Store at controlled room temperature, 20°-25°C (68°-77°F).

DO NOT REFRIGERATE.

Rx Only

Distributed by:
Meda Pharmaceuticals Inc.
Canonsburg, PA 15317 U.S.A.

© 2024 Mylan Specialty L.P., a Viatris Company

For Medical Inquiries, call toll-free 1-877-848-6608

CORTIFOAM is a registered trademark of Alaven Pharmaceutical LLC, a Viatris Company.

IN-683015-05
141280-0324

PRINCIPAL DISPLAY PANEL - 15 g Label

NDC 0037-6830-15

cortifoam®
(hydrocortisone acetate 10%)

rectal foam

Rx Only

15 g net wt

DIRECTIONS FOR USE

APPLICATOR

FOAM CONTAINER

1 Shake foam container vigorously for 5 - 10 seconds before each use. Do not remove container cap during use of the product.

2 Hold container upright on a level surface and gently place the tip of the applicator onto the nose of the container cap.

CONTAINER MUST BE HELD UPRIGHT TO OBTAIN PROPER FLOW OF MEDICATION.

3 Pull plunger past the fill line on the applicator barrel.

4 To fill applicator barrel, press down firmly on cap flanges, hold for 1 – 2 seconds and release. Pause 5 - 10 seconds to allow foam to expand in applicator barrel. Repeat until foam reaches fill line. Remove applicator from container cap. Allow some foam to remain on the applicator tip.
A burst of air may come out of container with first pump.

5 Hold applicator firmly by barrel, making sure thumb and middle finger are positioned securely underneath and resting against barrel wings. Place index finger over the plunger. Gently insert tip into anus. Once in place, push plunger to expel foam, then withdraw applicator.

6 After each use, applicator parts should be pulled apart for thorough cleaning with warm water. The container cap and underlying tip should also be pulled apart and rinsed to help prevent buildup of foam and possible blockage.

Description: cortifoam® (hydrocortisone acetate) 10% rectal foam contains hydrocortisone acetate 10% in a base containing propylene glycol, emulsifying wax, polyoxyethylene-10-stearyl ether, cetyl alcohol, methylparaben, propyl-paraben, trolamine, purified water and inert propellants: isobutane and propane.

Dosage: One applicatorful once or twice daily for two or three weeks, and every second day thereafter, administered rectally. See back of carton for full directions for use.

Please see package insert for further information. For rectal use only.

117756-0324 UC-683015-05

Caution: Do not insert any part of the aerosol container directly into the anus. Apply to anus only with the enclosed applicator.

WARNINGS: Contents of the container are under pressure. Do not burn or puncture the aerosol container. Do not store at temperatures above 120°F (49°C).

KEEP OUT OF REACH OF CHILDREN.

Store upright at controlled room temperature 20° - 25°C (68° - 77°F).

DO NOT REFRIGERATE

Distributed by: Meda Pharmaceuticals Inc., Canonsburg, PA 15317 U.S.A.

© 2024 Mylan Specialty L.P., a Viatris Company

CORTIFOAM is a registered trademark of Alaven Pharmaceutical LLC, a Viatris company.